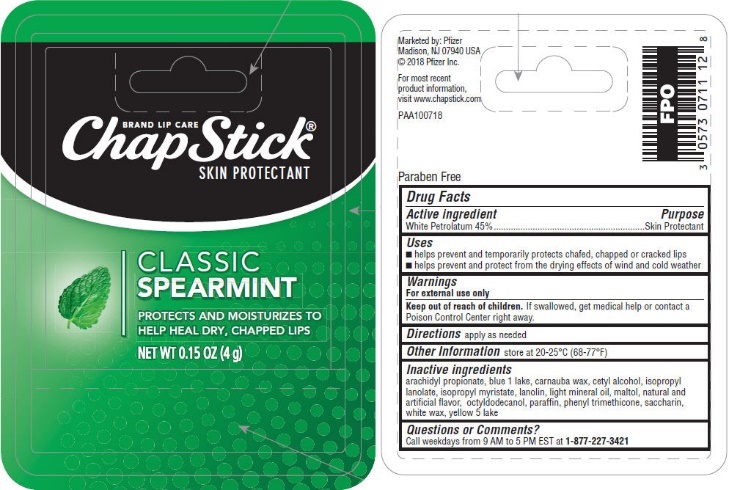 DRUG LABEL: ChapStick Classic Spearmint
NDC: 0573-0711 | Form: STICK
Manufacturer: Haleon US Holdings LLC
Category: otc | Type: HUMAN OTC DRUG LABEL
Date: 20240319

ACTIVE INGREDIENTS: PETROLATUM 450 mg/1 g
INACTIVE INGREDIENTS: ARACHIDYL PROPIONATE; FD&C BLUE NO. 1; CARNAUBA WAX; CETYL ALCOHOL; ISOPROPYL MYRISTATE; LANOLIN; LIGHT MINERAL OIL; MALTOL; OCTYLDODECANOL; PARAFFIN; PHENYL TRIMETHICONE; SACCHARIN; WHITE WAX; FD&C YELLOW NO. 5

Drug Facts

Active ingredient

White Petrolatum 45%

Purpose

Skin Protectant

Uses

- helps prevent and temporarily protects chafed, chapped or cracked lips
- helps prevent and protect from the drying effects of wind and cold weather

Warnings

For external use only

Keep out of reach of children. If swallowed, get medical help or contact a Poison Control Center right away.

Directions

apply as needed

Other Information

store at 20-25°C (68-77°F)

Inactive ingredients

arachidyl propionate, blue 1 lake, carnauba wax, cetyl alcohol, isopropyl lanolate, isopropyl myristate, lanolin, light mineral oil, maltol, natural and artificial flavor, octyldodecanol, paraffin, phenyl trimethicone, saccharin, white wax, yellow 5 lake

Questions or Comments?

Call weekdays from 9 AM to 5 PM EST at 1-877-227-3421

Additional information

Marketed by: Pfizer

Madison, NJ 07940 USA

©2018 Pfizer Inc.

For most recent product information, visit www.chapstick.com

Paraben Free

PRINCIPAL DISPLAY PANEL

BRAND LIP CARE
ChapStick®
SKIN PROTECTANT

CLASSIC
SPEARMINT

PROTECTS AND MOISTURIZES TO
HELP HEAL DRY, CHAPPED LIPS

NET WT 0.15 OZ (4 g)